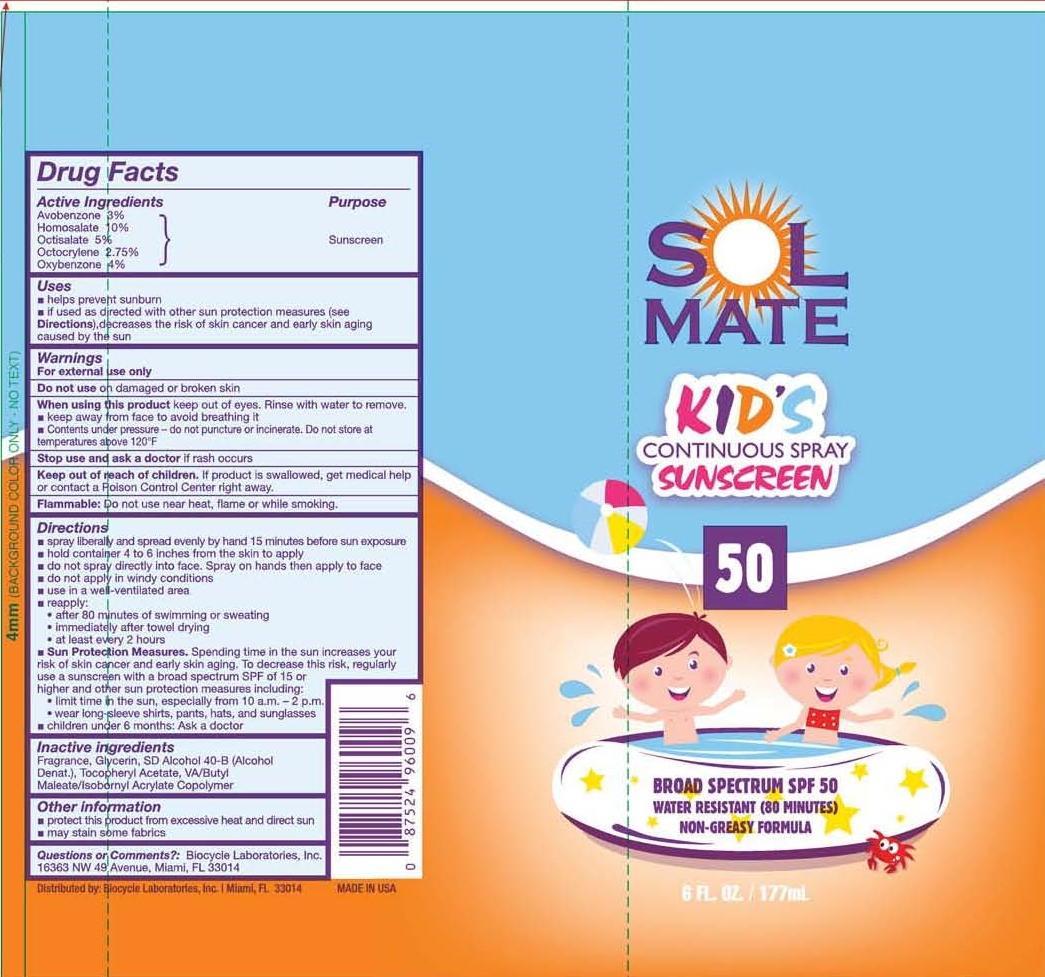 DRUG LABEL: SolMate
NDC: 13630-0058 | Form: SPRAY
Manufacturer: Prime Packaging, Inc.
Category: otc | Type: HUMAN OTC DRUG LABEL
Date: 20200117

ACTIVE INGREDIENTS: AVOBENZONE 25.4 mg/1 mL; HOMOSALATE 84.7 mg/1 mL; OCTISALATE 42.4 mg/1 mL; OCTOCRYLENE 23.3 mg/1 mL; OXYBENZONE 33.9 mg/1 mL
INACTIVE INGREDIENTS: GLYCERIN; .ALPHA.-TOCOPHEROL ACETATE; ALCOHOL

Active ingredients

Avobenzone 3 %, Homosalate 10 %, Octisalate 5 %, Octocrylene 2.75 %, and Oxybenzone 4 %

Purpose

Sunscreen

Uses

- helps prevent sunburn
- if used as directed with other sun protection measures (see Directions), decreases the risk of skin cancer and early skin aging caused by the sun

Warnings

OTHER SAFETY INFORMATION

For external use only

Do not use on damaged or broken skin.

When using this product keep out of eyes. Rinse with water to remove.

- keep away from face to avoid breathing it.
- Contents under pressure - do not puncture or incinerate. Do not store at temperatures above 120^0F

Stop use and ask a doctor if rash occurs.

Keep out of reach of children. If product is swallowed, get medical help or contact a Poison Control Center right away.

OTHER SAFETY INFORMATION

Flammable: Do not use near heat, flame or while smoking.

Directions

- spray liberally and spread evenly by hand 15 minutes before sun exposure
- hold container 4 to 6 inches from the skin to apply
- do not spray directly into face. Spray on hands then apply to face
- do not apply in windy conditions
- use in well-ventilated areas.
- reapply:
  - after 80 minutes of swimming or sweating
  - immediately after towel drying
  - at least every 2 hours
- Sun Protection Measures. Spending time in the sun increases your risk of skin cancer and early skin aging. To decrease this risk, regularly use a sunscreen with broad spectrum SPF of 15 or higher and other sun protection measures including:
  - limit time in the sun, especially from 10 a.m. – 2 p.m.
  - wear long-sleeve shirts, pants, hats, and sunglasses
- children under 6 months: Ask a doctor

Inactive Ingredients

Fragrance (Parfum), Glycerin, SD Alcohol 40-B (Alcohol Denat.), Tocopheryl Acetate, VA/Butyl Maleate/Isobornyl Acrylate Copolymer

Other information

- protect this product from excesive heat and direct sun
- may stain some fabrics

Questions or Comments? Biocycle Laboratories, Inc.

16363 NW 49th Avenue, Miami, FL 33014

PRINCIPAL DISPLAY PANEL - 177 mL Can Label

SOL

MATE

KID'S

CONTINUOUS SPRAY

SUNSCREEN

50

BROAD SPECTRUM SPF 50

WATER RESISTANT (80 MINUTES)

NON-GREASY FORMULA

6 FL. OZ. / 177 mL